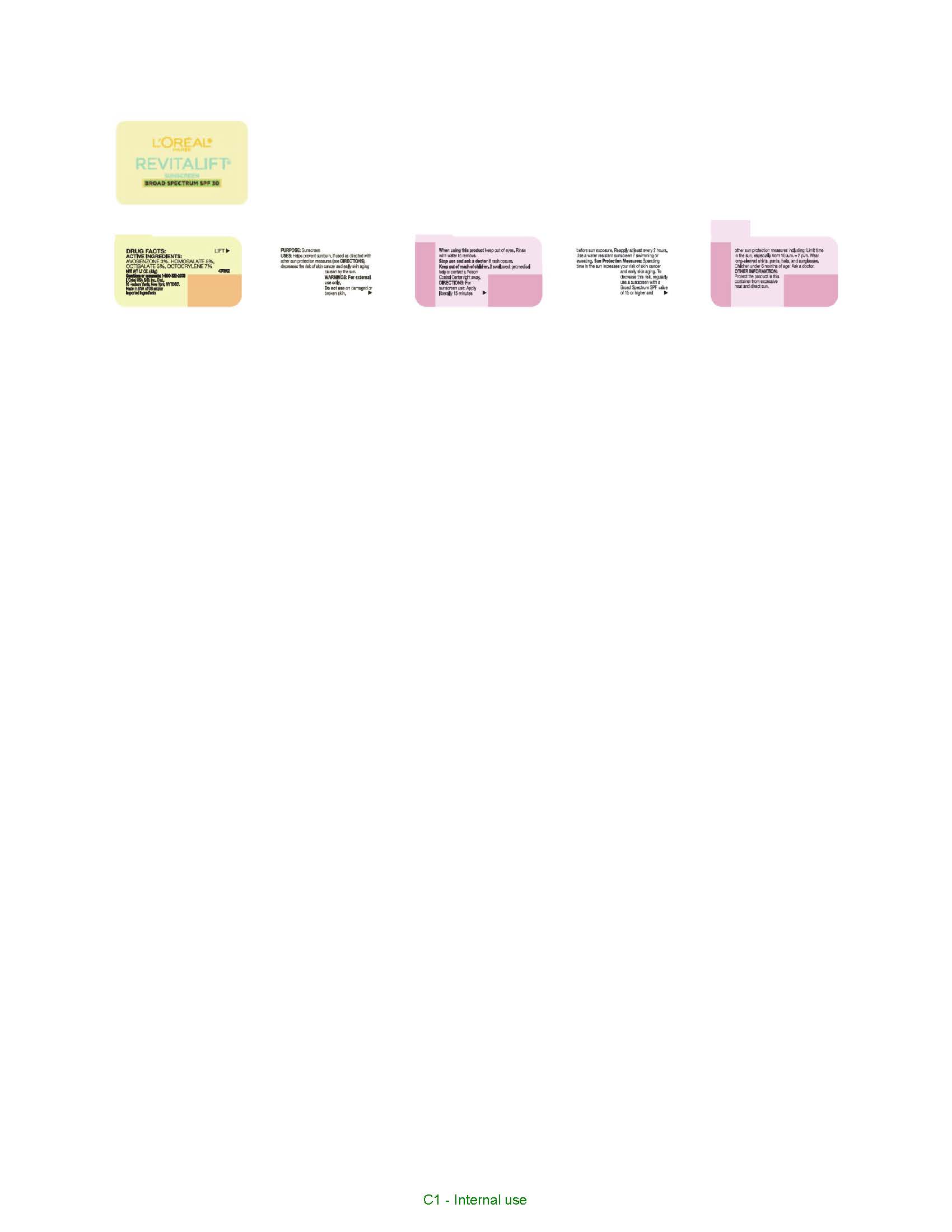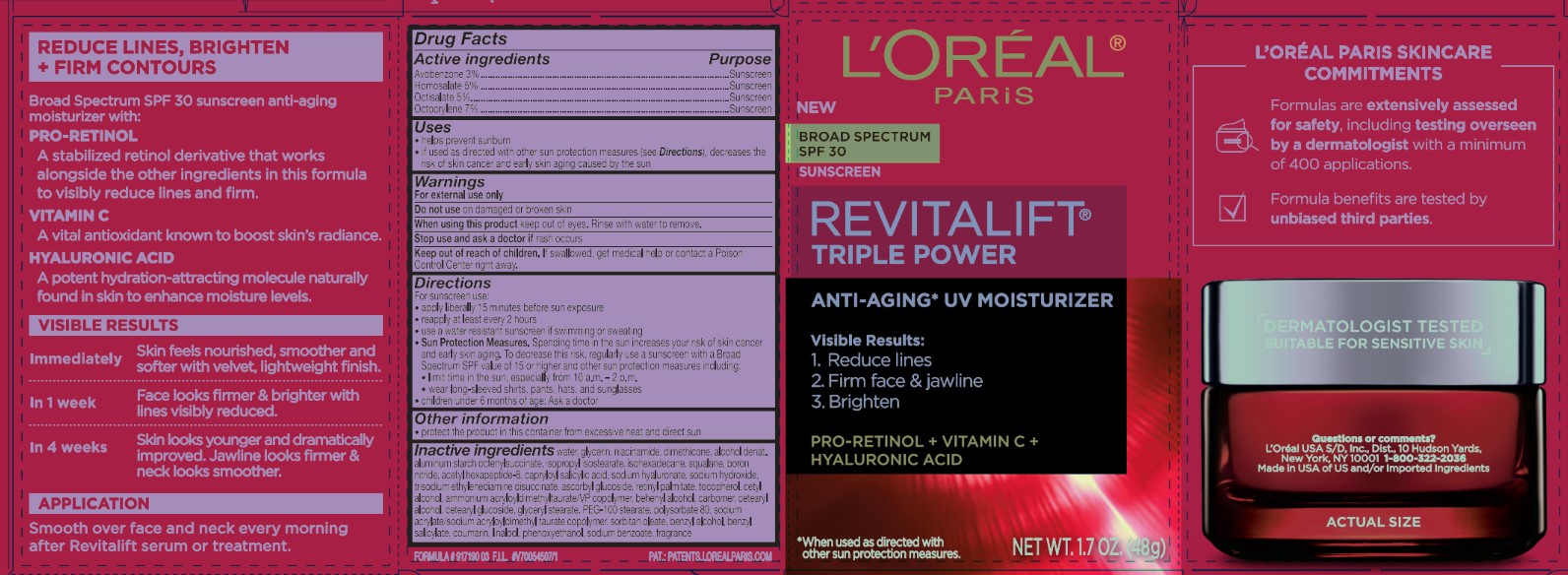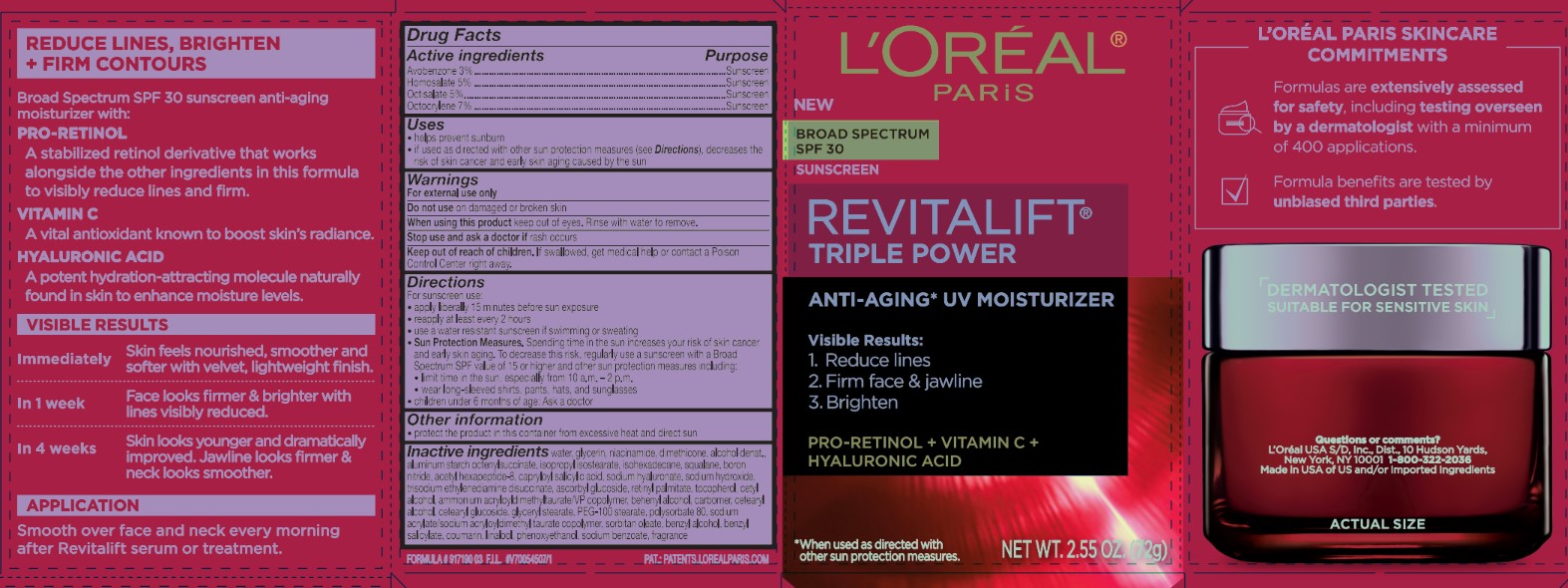 DRUG LABEL: LOreal Paris Revitalift Triple Power Anti Aging Moisturizer Broad Spectrum SPF 30 Sunscreen
NDC: 49967-341 | Form: CREAM
Manufacturer: L’Oreal USA Products Inc
Category: otc | Type: HUMAN OTC DRUG LABEL
Date: 20241223

ACTIVE INGREDIENTS: AVOBENZONE 30 mg/1 g; HOMOSALATE 50 mg/1 g; OCTISALATE 50 mg/1 g; OCTOCRYLENE 70 mg/1 g
INACTIVE INGREDIENTS: WATER; GLYCERIN; NIACINAMIDE; DIMETHICONE; ALUMINUM STARCH OCTENYLSUCCINATE; ISOPROPYL ISOSTEARATE; ISOHEXADECANE; SQUALANE; BORON NITRIDE; ACETYL HEXAPEPTIDE-8; CAPRYLOYL SALICYLIC ACID; SODIUM HYALURONATE; SODIUM HYDROXIDE; TRISODIUM ETHYLENEDIAMINE DISUCCINATE; ASCORBYL GLUCOSIDE; RETINYL PALMITATE; TOCOPHEROL; CETYL ALCOHOL; AMMONIUM ACRYLOYLDIMETHYLTAURATE/VP COPOLYMER; BEHENYL ALCOHOL; CETEARYL ALCOHOL; CETEARYL GLUCOSIDE; GLYCERYL STEARATE; PEG-100 STEARATE; POLYSORBATE 80; SODIUM ACRYLATE/SODIUM ACRYLOYLDIMETHYLTAURATE COPOLYMER (4000000 MW); SORBITAN OLEATE; BENZYL ALCOHOL; BENZYL SALICYLATE; COUMARIN; LINALOOL; PHENOXYETHANOL; SODIUM BENZOATE

Drug Facts

Active ingredients

Avobenzone 3%

Homosalate 5%

Octisalate 5%

Octocrylene 7%

Purpose

Sunscreen

Uses

- helps prevent sunburn
- if used as directed with other sun protection measures (see Directions), decreases the risk of skin cancer and early skin aging caused by the sun

Warnings

For external use only

Do not use

on damaged or broken skin

When using this product

keep out of eyes. Rinse with water to remove.

Stop use and ask a doctor if

rash occurs

Keep out of reach of children.

If swallowed, get medical help or contact a Poison Control Center right away.

Directions

- For sunscreen use:
  • apply liberally 15 minutes before sun exposure
  • reapply at least every 2 hours
  • use a water resistant sunscreen if swimming or sweating
- Sun Protection Measures. Spending time in the sun increases your risk of skin cancer and early skin aging. To decrease this risk, regularly use a sunscreen with a Broad Spectrum SPF value of 15 or higher and other sun protection measures including:
  o limit time in the sun, especially from 10 a.m. - 2 p.m.
  o wear long-sleeved shirts, pants, hats, and sunglasses
- children under 6 months of age: Ask a doctor

Other information

- protect the product in this container from excessive heat and direct sun

Inactive ingredients

water, glycerin, niacinamide, dimethicone, alcohol denat., aluminum starch octenylsuccinate, isopropyl isostearate, isohexadecane, squalane, boron nitride, acetyl hexapeptide-8, capryloyl salicylic acid, sodium hyaluronate, sodium hydroxide, trisodium ethylenediamine disuccinate, ascorbyl glucoside, retinyl palmitate, tocopherol, cetyl alcohol, ammonium acryloyldimethyltaurate/VP copolymer, behenyl alcohol, carbomer, cetearyl alcohol, cetearyl glucoside, glyceryl stearate, PEG-100 stearate, polysorbate 80, sodium acrylate/sodium acryloyldimethyl taurate copolymer, sorbitan oleate, benzyl alcohol, benzyl salicylate, coumarin, linalool, phenoxyethanol, sodium benzoate, fragrance